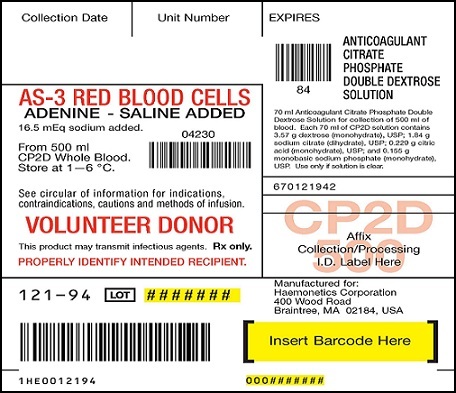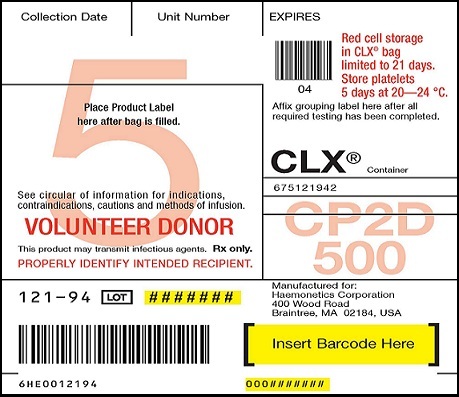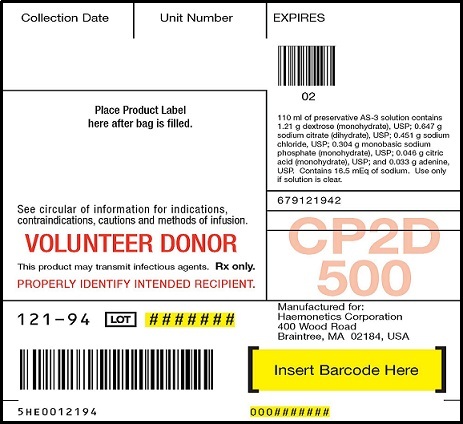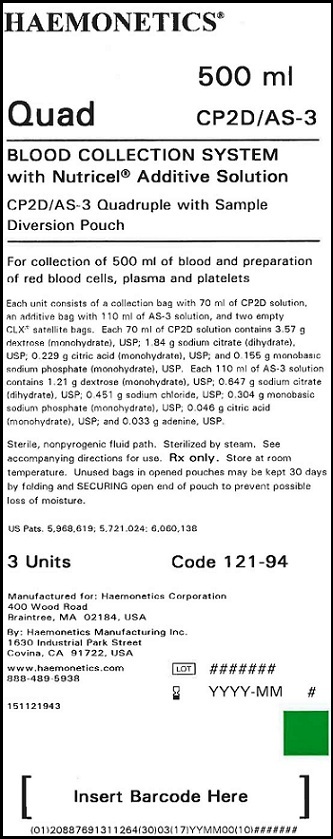 DRUG LABEL: Nutricel Additive Solution - CP2D
NDC: 53157-100 | Form: SOLUTION
Manufacturer: Haemonetics Manufacturing Inc.
Category: prescription | Type: HUMAN PRESCRIPTION DRUG LABEL
Date: 20130913

ACTIVE INGREDIENTS: DEXTROSE 3.57 g/70 mL
INACTIVE INGREDIENTS: CITRIC ACID MONOHYDRATE; SODIUM PHOSPHATE, MONOBASIC, MONOHYDRATE

CP2D/AS-3 Blood Collection and Sampling System

DESCRIPTION

CP2D/AS-3 Blood Collection and Sampling System – Nutricel Additive System

Instruction for Use for Systems Containing a Y Sampling Site (YSS) or Sample Diversion Pouch (with or without a pre-attached SampLok® Vacuum Tube Holder).

Refer to unit foil package label for specific product description being used.

Sterile, nonpyrogenic fluid path. Sterilized by steam.

Rx only

This product is free of natural rubber latex.

INDICATIONS AND USAGE

For collection of blood and preparation of red blood cells, plasma and platelets.

WARNINGS

Failure to achieve and maintain a closed system during processing would result in a product that must be transfused within 24 hours.

GENERAL PRECAUTIONS

Use aseptic technique. Use only if solutions are clear. If preparing a platelet concentrate, the platelet-rich plasma should be separated from the red blood cells within 8 hours after blood collection. If preparing fresh frozen plasma, separate from the red blood cells and place in the freezer at -18 °C or colder within 8 hours after collection.

* During processing, always observe the following precautions:

1. Sealing should be done in a manner that avoids fluid splatter.

2. Always dispose of blood-contaminated products in a manner consistent with established BIOHAZARD safety procedures.

STORAGE

Store CP2D/AS-3 preserved red blood cells at 1—6 °C for up to 42 days and use as indicated.

I. BLOOD COLLECTION INSTRUCTIONS FOR SYSTEMS CONTAINING A Y SAMPLING SITE(YSS) ONLY

1. Load blood agitation device or suspend blood bag on donor scale and adjust donor scale to desired collection gross weight as per manufacturer's instructions.

2. Clamp donor tubing between DonorCare® Needle Guard (DCNG) and Y Sampling Site.

3. Secure donor tubing above the Y connector and disinfect site of phlebotomy.

4. If using blood pressure cuff, inflate to not more than 60 mm Hg.

5. Remove donor needle cover and accomplish phlebotomy.

6. Release clamp and ensure there is blood flow. Reduce pressure as required.

7. Slide the DCNG midway over the needle hub and securely tape DCNG to the donor's arm as close to the top of the DCNG as possible. Note: If blood flow is slow, slide DCNG away from the needle hub, adjust and re-engage DCNG. If repeated needle adjustment is necessary, slide DCNG away from the needle hub and re-engage at the end of blood collection.

8. Collect appropriate volume of blood into collection bag, as indicated on packaging.

Note: Mix blood and anticoagulant frequently during collection, for example, once every 45 seconds, and immediately after collection. If blood agitation device is used, follow manufacturer's operating instructions.

9. After required amount of blood has been collected, seal donor tubing close to Y Sampling Site.*

10. For blood sampling, remove the Y Sampling Site needle cover. Ensure the protective sheath is in place over the sampling needle.

11. Fasten the vacuum tube holder on to the base of the sampling needle.

12. Collect blood samples into vacuum tubes.

13. Ensure the vacuum tubes are centered within the vacuum tube holder during sample collection.

14. Maintain forward pressure on the vacuum tubes during sample collection. Note: After the last tube is collected, it is recommended that the vacuum tube holder be left in place.

15. After blood samples are collected, clamp donor tubing between the Y Sampling Site and DCNG, and as close to the DCNG as possible.

16. Release any remaining pressure from the donor's arm.

17. DCNG must be held stationary while the needle is withdrawn into it. While holding sides of DCNG near the front, grasp the tubing below the clamp and pull the needle into the DCNG until it locks into place, and the needle hub engages the bottom of the DCNG.

18. Insert the DCNG into the vacuum tube holder. Note: It is recommended that the DCNG be inserted securely into the vacuum tube holder, prior to discarding.

19. Seal donor tubing adjacent to DCNG.* Detach and discard needle, DCNG,Y Sampling Site and tubing.*

20. Strip tubing between seal and collection bag.

21. Continue to “Processing Instructions”, Section IV, Step 1.

II. BLOOD COLLECTION INSTRUCTION FOR SYSTEMS CONTAINING A SAMPLE DIVERSION POUCH WITH OR WITHOUT A PRE-ATTACHED SAMPLOK® VACUUM TUBE HOLDER

When using systems with a pre-attached SampLok vacuum tube holder, follow instructions as noted below, but refer to Section III when indicated to do so.

1. Load blood agitation device or suspend blood bag on donor scale and adjust donor scale to desired collection gross weight as per manufacturer's instructions.

2. Clamp donor tubing between DonorCare Needle Guard (DCNG) and Sampling Site.

3. Secure donor tubing above the Y connector and disinfect site of phlebotomy.

4. If using blood pressure cuff, inflate to not more than 60 mm Hg.

5. Remove donor needle cover and accomplish phlebotomy.

6. Release clamp and ensure there is blood flow.

7. Slide the DCNG midway over the needle hub and securely tape DCNG to the donor's arm as close to the top of the DCNG as possible. Note: If blood flow is slow, slide DCNG away from the needle hub, adjust and re-engage DCNG. If repeated needle adjustment is necessary, slide DCNG away from the needle hub and re-engage at the end of blood collection.

8. The donor blood will be automatically diverted to the sample diversion pouch. Once the sample diversion pouch is filled, close clamp immediately on tubing between the sample diversion pouch and Y connector. Warning: To avoid risk of air embolism to donor, do not squeeze sample diversion pouch while tubing is open.

9. Open snap-open closure between the Y connector and the collection bag to initiate blood collection. Reduce pressure as needed.

10. Permanently seal tubing between the sample diversion pouch and the Y connector to maintain sterility of the system prior to collecting blood samples.* Note: When using systems with a pre-attached SampLok vacuum tube holder, go to Section III.

11. For blood sampling, remove the Sampling Site needle cover. Ensure the protective sheath is in place over the sampling needle.

12. Fasten the vacuum tube holder on to the base of the sampling needle.

13. Position the sample diversion pouch downwards so that the air rises to the top of the pouch and away from the vacuum tube holder. Note: Drawing air into the vacuum tube may cause hemolysis.

14. Collect blood samples from the sample diversion pouch into vacuum tubes within approximately four minutes to avoid possible clot formation.

15. Ensure the vacuum tubes are centered within the vacuum tube holder during sample collection.

16. Maintain forward pressure on the vacuum tubes during sample collection. Note: After the last tube is collected, it is recommended that the vacuum tube holder be left in place.

17. Collect appropriate volume of blood into collection bag as indicated on packaging. Note: Mix blood and anticoagulant frequently during collection, for example, once every 45 seconds, and immediately after collection. If blood agitation device is used, follow manufacturer's operating instructions.

18. After required amount of blood has been collected, seal donor tubing close to snap-open closure.*

19. Clamp donor tubing between the Y connector and DCNG, as close as possible to the DCNG.

20. Release any remaining pressure from donor's arm.

21. DCNG must be held stationary while the needle is withdrawn into it. While holding sides of DCNG near the front, grasp the tubing below the clamp and pull the needle into the DCNG until it locks into place, and the needle hub engages the bottom of the DCNG.

22. Insert the DCNG into the vacuum tube holder, if desired. Note: It is recommended that the DCNG be inserted securely into the vacuum tube holder, prior to discarding.

23. Seal donor tubing adjacent to DCNG.* Detach and discard needle, DCNG, sample diversion pouch and tubing.*

24. Strip tubing between seal and collection bag.

25. Continue to “Processing Instructions”, Section IV, Step 1.

III. WHEN USING SYSTEMS WITH A PRE-ATTACHED SAMPLOK® VACUUM TUBE HOLDER

1. To collect blood samples, open lid from SampLok vacuum tube holder.

2. Open snap-open closure between sample diversion pouch and SampLok vacuum tube holder.

3. Position the sample diversion pouch downwards so that the air rises to the top of the pouch and away from the SampLok vacuum tube holder. Note: Drawing air into the vacuum tube may cause hemolysis.

4. Collect blood samples from the sample diversion pouch into vacuum tubes within approximately four minutes to avoid possible clot formation.

5. Ensure the vacuum tubes are centered within the SampLok vacuum tube holder during sample collection.

6. Maintain forward pressure on the vacuum tubes during sample collection.

7. The lid may be closed on the SampLok vacuum tube holder after sample collection.

8. Return to Section II, Step 17. Note: When collection of unit is complete, and the donor needle is engaged in the DCNG, open the lid of the SampLok vacuum tube holder and insert the DCNG into the holder. Twist until it locks into place. An audible click will confirm that it is locked

IV. PROCESSING INSTRUCTIONS

1. Process whole blood within 72 hours of collection.

2. Mix whole blood/anticoagulant thoroughly.

3. Load whole blood and satellite bags into centrifuge cup, ensuring that the tubing stays in the top half of the cup.

4. Centrifuge at appropriate conditions to produce desired components.

5. Carefully remove the unit from the centrifuge and place the red cell storage bag in the plasma expressor.

6. Clamp tubing to extra satellite bags, if present.

7. Gently apply expressor pressure.

8. Open snap-open closure to satellite bag and express plasma.

9. After plasma is expressed, clamp tubing between red cell storage bag and Y connector, and release expressor pressure.

10. Clamp tubing between the Y connector and plasma bag.

11. Hang AS-3 bag above red cell storage bag and remove clamp from tubing to the red cell storage bag.

12. Open snap-open closure on the bag containing the AS-3 additive solution and transfer to the bag containing the red cells. Note: AS-3 solution should be added to the packed red blood cells immediately after removal of plasma.

Transfer AS-3 solution under one of the following processing conditions:

a. within 8 hours of collection if whole blood is held at room temperature.

b. within 72 hours of collection if whole blood is refrigerated.

13. Seal tubing and detach the bag containing packed red cells, and set aside plasma for further processing.*

14. Gently mix packed red cells and AS-3 solution.

15. Store CP2D/AS-3 preserved red blood cells at 1—6 °C for up to 42 days and use as indicated. Note: If AS-3 is not used, whole blood or red blood cells in CP2D alone may be stored at 1—6 °C for up to 21 days.

HOW SUPPLIED

Each shipping case contains 8 foil envelopes. Within each foil envelope resides 3 clear pouches containing an individual collection system. Each unit consists of a collection bag with 70ml of CP2D solution, an additive bag with 110ml of AS-3 solution, and two empty CLX bags.

PRINCIPAL DISPLAY PANEL

AS-3 RED BLOOD CELLS ADENINE-SALINE ADDED 16.5 mEq sodium added

From 500ml CP2D Whole Blood Store at 1—6 °C

Anticoagulant Citrate Phosphate Double Dextrose Solution

70ml Anticoagulant Citrate Phosphate Double Dextrose Solution for collection of 500ml of blood. Each 70ml of CP2D solution contains 3.57g dextrose (monohydrate), USP; 1.84g sodium citrate (dihydrate), USP; 0.229g citric acid (monohydrate), USP; and 0.155g monobasic sodium phosphate (monohydrate), USP. Use only if solution is clear.

See circular of information for indications, contraindications, cautions and methods of infusion. VOLUNTEER DONOR. This product may transmit infectious agents. Rx only. PROPERLY IDENTIFY INTENDED RECIPIENT.

CP2D 500

121-94

Red cell storage in CLX bag limited to 21 days. Store platelets 5 days at 20—24°C

CLX Container CP2D 500

See circular of information for indications, contraindications, cautions and methods of infusion. VOLUNTEER DONOR. This product may transmit infectious agents. Rx only. PROPERLY IDENTIFY INTENDED RECIPIENT.

121-94

110ml of preservative AS-3 solution contains 1.21g dextrose (monohydrate), USP; 0.647 g sodium chloride (dihydrate), USP; 0.451 g sodium chloride USP; 0.304 g monobasic sodium phosphate (monohydrate), USP; and 0.033g adenine, USP. Contains 16.5 mEq of sodium.

Use only if solution is clear.

See circular of information for indications, contraindications, cautions and methods of infusion. VOLUNTEER DONOR. This product may transmit infectious agents. Rx only. PROPERLY IDENTIFY INTENDED RECIPIENT.

121-94

CP2D/AS-3 500ml QUAD

BLOOD COLLECTION SYSTEM with Nutricel Additive Solution

CP2D/AS-3 Quadruple with Sample Diversion Pouch

For collection of 500ml of blood and preparation of red blood cells, plasma and platelets

Each unit consists of a collection bag with 70ml of CP2D solution, an additive bag with 110ml of AS-3 solution, and two empty CLX satellite bags. Each 70ml of CP2D solution contains 3.57 g dextrose (monohydrate), USP; 1.84g sodium citrate (dihydrate), USP; 0.229 g citric acid (monohydrate), USP; and 0.155g monobasic sodium phosphate (monohydrate), USP. Each 110ml of AS-3 solution contains 1.21 g dextrose (monohydrate), USP; 0.647 g sodium citrate (dihydrate), USP; 0.451 g sodium chloride, USP; 0.304 g monobasic sodium phosphate (monohydrate), USP; 0.046 g citric acid (monohydrate), USP; and 0.033 g adenine, USP.

Sterile, non pyrogenic fluid path. Sterilized by steam. See accompanying directions for use. Rx only. Store at room temperature. Unused bags in opened pouches may be kept 30 days by folding and SECURING open end of pouch to prevent possible loss of moisture.

3 Units Code 121-94

REFERENCES

HAEMONETICS, THE Blood Management Company and Nutricel are registered trademarks of Haemonetics Corporation. DonorCare and SampLok are registered trademarks of ITL Corporation, Canberra, Australia.

MANUFACTURER

Manufactured for: Haemonetics Corporation

400 Wood Road

Braintree, MA 02184, USA

By: Haemonetics Manufacturing Inc

1630 Industrial Park Street

Covina, CA 91722, USA

Visit us at www.haemonetics.com

Phone: 888.489.593